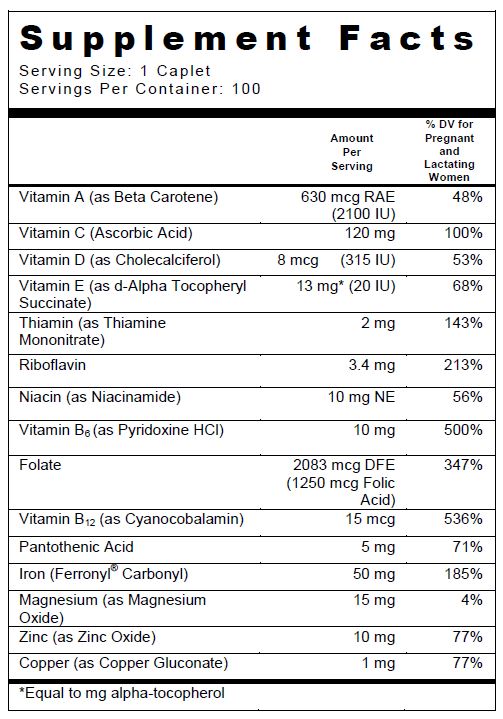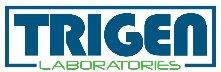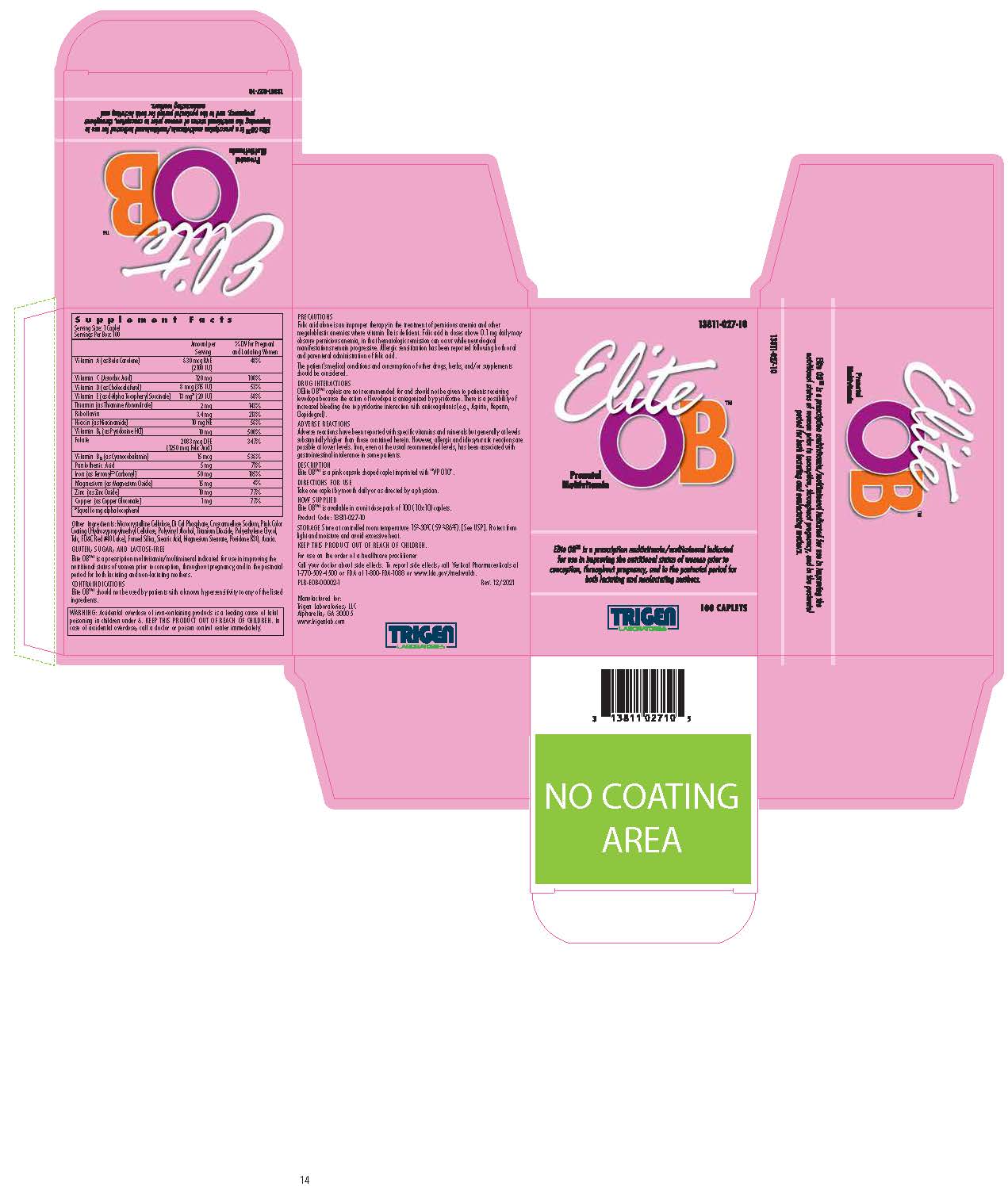 DRUG LABEL: Elite OB
NDC: 13811-027 | Form: TABLET
Manufacturer: Trigen Laboratories, LLC
Category: other | Type: DIETARY SUPPLEMENT
Date: 20211230

ACTIVE INGREDIENTS: VITAMIN A 2100 [iU]/1 1; THIAMINE 2 mg/1 1; RIBOFLAVIN 3.40 mg/1 1; PYRIDOXINE HYDROCHLORIDE 10 mg/1 1; CYANOCOBALAMIN 15 ug/1 1; FOLIC ACID 1.25 mg/1 1; VITAMIN D 315 [iU]/1 1; ASCORBIC ACID 120 mg/1 1; .ALPHA.-TOCOPHEROL SUCCINATE, D- 20 [iU]/1 1; NIACINAMIDE 10 mg/1 1; PANTOTHENIC ACID 5 mg/1 1; COPPER 1 mg/1 1; MAGNESIUM OXIDE 15 mg/1 1; ZINC OXIDE 10 mg/1 1; Iron 50 mg/1 1
INACTIVE INGREDIENTS: CELLULOSE, MICROCRYSTALLINE; CALCIUM PHOSPHATE, DIBASIC, ANHYDROUS; CROSCARMELLOSE SODIUM; HYPROMELLOSES; TITANIUM DIOXIDE; SILICON DIOXIDE; STEARIC ACID; MAGNESIUM STEARATE; POVIDONE K30; ACACIA; POLYETHYLENE GLYCOL, UNSPECIFIED; ETHYLCELLULOSES; TALC; MINERAL OIL; FD&C RED NO. 40; POLYVINYL ALCOHOL, UNSPECIFIED

Elite OBTM

SUPPLEMENT FACTS

Other Ingredients: Microcrystalline Cellulose, Di Cal Phosphate, Croscarmellose Sodium, Pink Color Coating (Hydroxypropylmethyl Cellulose, Polyvinyl Alcohol, Titanium Dioxide, Polyethylene Glycol, Talc, FD&C Red #40 Lake), Fumed Silica, Stearic Acid, Magnesium Stearate, Povidone K30, Acacia.

GLUTEN, SUGAR, AND LACTOSE FREE

Elite OB™ is a prescription multivitamin/multimineral indicated for use in improving the nutritional status of women prior to conception, throughout pregnancy, and in the postnatal period for both lactating and non-lactating mothers.

CONTRAINDICATIONS

Elite OB™ should not be used by patients with a known hypersensitivity to any of the listed ingredients.

WARNINGS

WARNING: Accidental overdose of iron-containing products is a leading cause of fatal poisoning in children under 6. KEEP THIS PRODUCT OUT OF THE REACH OF CHILDREN. In case of accidental overdose, call a doctor or poison control center immediately.

PRECAUTIONS

Folic acid alone is an improper therapy in the treatment of pernicious anemia and other megaloblastic anemias where vitamin B12 is deficient. Folic acid in doses above 0.1 mg daily may obscure pernicious anemia, in that hematologic remission can occur while neurological manifestations remain progressive. Allergic sensitization has been reported following both oral and parenteral administration of folic acid.

The patient’s medical conditions and consumption of other drugs, herbs, and/or supplements should be considered.

DRUG INTERACTIONS

Elite OB™ caplets are not recommended for and should not be given to patients receiving levodopa because the action of levodopa is antagonized by pyridoxine. There is a possibility of increased bleeding due to pyridoxine interaction with anticoagulants (e.g., Aspirin, Heparin, Clopidogrel).

ADVERSE REACTIONS

Adverse reactions have been reported with specific vitamins and minerals but generally at levels substantially higher than those contained herein. However, allergic and idiosyncratic reactions are possible at lower levels. Iron, even at the usual recommended levels, has been associated with gastrointestinal intolerance in some patients.

DESCRIPTION

Elite OB™ is a pink capsule shaped caplet imprinted with "VP 010".

DIRECTIONS FOR USE

Take one caplet by mouth daily or as directed by a physician.

HOW SUPPLIED

Elite OBTM is available as a pink capsule shaped caplet. Available in unit-dose pack of 100 (10x10)

STORAGE

Store at controlled room temperature 15º-30ºC (59º-86ºF). [See USP]. Protect from light and moisture and avoid excessive heat.

KEEP OUT OF REACH OF CHILDREN.

For use on the order of a healthcare practitioner.

Call your doctor about side effects. To report side effects, call Trigen Laboratories, LLC at 1-770-509-4500 or FDA at 1-800-FDA-1088 or www.fda.gov/medwatch.

PLR-EOB-00002-1 Rev. 12/2021

Manufactured for:

Trigen Laboratories, LLC

Alpharetta, GA 30005

www.trigenlab.com

PRINCIPAL DISPLAY PANEL - 100 tablet label

13811-027-10

Elite OBTM

Prenatal
Multivitamin

TRIGEN
LABORATORIES